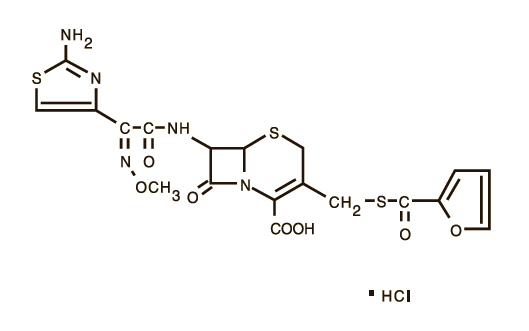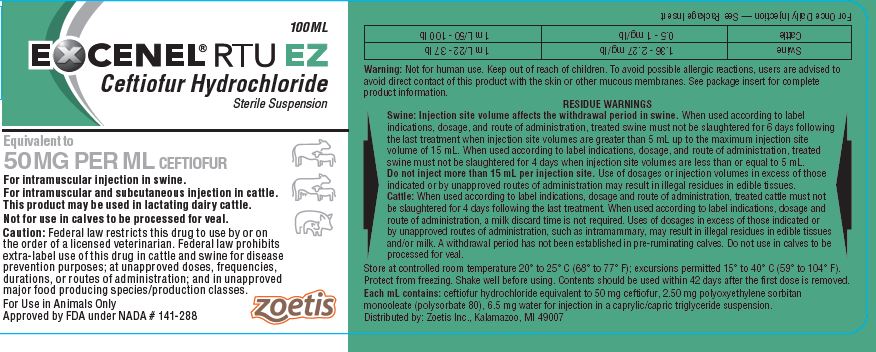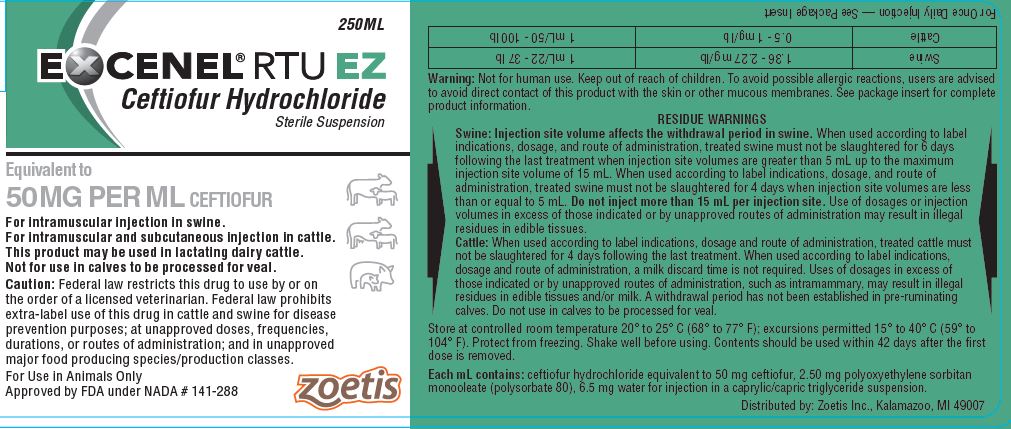 DRUG LABEL: Excenel
NDC: 54771-5402 | Form: INJECTION, SUSPENSION
Manufacturer: Zoetis Inc.
Category: animal | Type: PRESCRIPTION ANIMAL DRUG LABEL
Date: 20221005

ACTIVE INGREDIENTS: ceftiofur hydrochloride 50 mg/1 mL
INACTIVE INGREDIENTS: polysorbate 80

EXCENEL® RTU EZ
Ceftiofur Hydrochloride Sterile Suspension

For intramuscular injection in swine.
For intramuscular and subcutaneous injection in cattle. This product may be used in lactating dairy cattle.
Not for use in calves to be processed for veal.

CAUTION

Federal law restricts this drug to use by or on the order of a licensed veterinarian. Federal law prohibits extra-label use of this drug in cattle and swine for disease prevention purposes; at unapproved doses, frequencies, durations, or routes of administration; and in unapproved major food producing species/production classes.

DESCRIPTION

EXCENEL RTU EZ Sterile Suspension is a ready to use formulation that contains the hydrochloride salt of ceftiofur, which is a broad spectrum cephalosporin antibiotic. Each mL of this ready-to-use sterile suspension contains ceftiofur hydrochloride equivalent to 50 mg ceftiofur, 2.50 mg polyoxyethylene sorbitan monooleate (polysorbate 80), 6.5 mg water for injection in a caprylic/capric triglyceride suspension.

Figure 1. Structure:

Chemical Name of Ceftiofur Hydrochloride: 5-Thia-1-azabicyclo[4,2.0] oct-2-ene-2-carboxylic acid, 7-[[(2-amino-4-thiazolyl)(methoxyimino)-acetyl] amino]-3-[[(2-furanylcarbonyl)thio]methyl]-8-oxo-,hydrochloride salt [6R-[6α,7β(Z)]]-

INDICATIONS

Swine:

EXCENEL RTU EZ Sterile Suspension is indicated for treatment/ control of swine bacterial respiratory disease (swine bacterial pneumonia) associated with Actinobacillus pleuropneumoniae, Pasteurella multocida, Salmonella Choleraesuis and Streptococcus suis.

Cattle:

EXCENEL RTU EZ Sterile Suspension is indicated for treatment of the following bacterial diseases:

— Bovine respiratory disease (BRD, shipping fever, pneumonia) associated with Mannheimia haemolytica, Pasteurella multocida and Histophilus somni.

— Acute bovine interdigital necrobacillosis (foot rot, pododermatitis) associated with Fusobacterium necrophorum and Bacteroides melaninogenicus.

— Acute metritis (0 to 14 days post-partum) associated with bacterial organisms susceptible to ceftiofur.

DOSAGE AND ADMINISTRATION

Shake well before using.

Swine:

Administer intramuscularly at a dosage of 1.36 to 2.27 mg ceftiofur equivalents (CE)/lb (3 to 5 mg CE/kg) body weight (BW) (1 mL of sterile suspension per 22 to 37 lb BW). Treatment should be repeated at 24 hour intervals for a total of three consecutive days. Do not inject more than 15 mL per injection site.

Cattle:

— For bovine respiratory disease and acute bovine interdigital necrobacillosis: administer by intramuscular or subcutaneous administration at the dosage of 0.5 to 1 mg CE/lb (1.1 to 2.2 mg CE/kg) BW (1 to 2 mL sterile suspension per 100 lb BW). Administer daily at 24 hour intervals for a total of three consecutive days. Additional treatments may be administered on Days 4 and 5 for animals which do not show a satisfactory response (not recovered) after the initial three treatments. In addition, for BRD only, administer intramuscularly or subcutaneously 1 mg CE/lb (2.2 mg CE/kg) BW every other day on Days 1 and 3 (48 hour interval). Do not inject more than 15 mL per injection site.

Selection of dosage level (0.5 to 1 mg CE/lb) and regimen/duration (daily or every other day for BRD only) should be based on an assessment of the severity of disease, pathogen susceptibility and clinical response.

— For acute post-partum metritis: administer by intramuscular or subcutaneous administration at the dosage of 1 mg CE/lb (2.2 mg CE/kg) BW (2 mL sterile suspension per 100 lb BW). Administer at 24 hour intervals for five consecutive days. Do not inject more than 15 mL per injection site.

CONTRAINDICATIONS

As with all drugs, the use of EXCENEL RTU EZ Sterile Suspension is contraindicated in animals previously found to be hypersensitive to the drug.

WARNINGS

NOT FOR HUMAN USE. KEEP OUT OF REACH OF CHILDREN.

Penicillins and cephalosporins can cause allergic reactions in sensitized individuals. Topical exposures to such antimicrobials, including ceftiofur, may elicit mild to severe allergic reactions in some individuals. Repeated or prolonged exposure may lead to sensitization. Avoid direct contact of the product with the skin, eyes, mouth and clothing.

Persons with a known hypersensitivity to penicillin or cephalosporins should avoid exposure to this product.

In case of accidental eye exposure, flush with water for 15 minutes. In case of accidental skin exposure, wash with soap and water. Remove contaminated clothing. If allergic reaction occurs (e.g., skin rash, hives, difficult breathing), seek medical attention.

The safety data sheet contains more detailed occupational safety information. To obtain a safety data sheet (SDS) or to report any adverse event please call 1-888-963-8471.

For additional information about adverse drug experience reporting for animal drugs, contact FDA at 1-888-FDA-VETS or online at http://www.fda.gov/AnimalVeterinary/SafetyHealth.

CONTACT INFORMATION

For a copy of the Safety Data Sheet or to report adverse reactions, call Zoetis Inc. at 1-888-963-8471. For additional information about adverse drug experience reporting for animal drugs, contact FDA at 1-888-FDA-VETS or www.fda.gov/reportanimalae.

RESIDUE WARNINGS:

Swine:

Injection site volume affects the withdrawal period in swine. When used according to label indications, dosage, and route of administration, treated swine must not be slaughtered for 6 days following the last treatment when injection site volumes are greater than 5 mL up to the maximum injection site volume of 15 mL. When used according to label indications, dosage, and route of administration, treated swine must not be slaughtered for 4 days when injection site volumes are less than or equal to 5 mL. Do not inject more than 15 mL per injection site. Use of dosages or injection volumes in excess of those indicated or by unapproved routes of administration may result in illegal residues in edible tissues.

Cattle:

When used according to label indications, dosage and route of administration, treated cattle must not be slaughtered for 4 days following the last treatment. When used according to label indications, dosage and route of administration, a milk discard time is not required. Uses of dosages in excess of those indicated or by unapproved routes of administration, such as intramammary, may result in illegal residues in edible tissues and/or milk. A withdrawal period has not been established in pre-ruminating calves. Do not use in calves to be processed for veal.

PRECAUTIONS

The effects of ceftiofur on cattle and swine reproductive performance, pregnancy and lactation have not been determined.

Intramuscular and subcutaneous injection in cattle and intramuscular injection in swine can cause a transient local tissue reaction that may result in trim loss of edible tissue at slaughter.

CLINICAL PHARMACOLOGY

Swine:

Ceftiofur administered as either ceftiofur sodium or ceftiofur hydrochloride is metabolized rapidly to desfuroylceftiofur, the primary metabolite. Administration of ceftiofur to swine as either the sodium or hydrochloride salt provides effective concentrations of ceftiofur and desfuroylceftiofur metabolites in plasma above the lowest minimum inhibitory concentration to encompass 90% of the most susceptible isolates (MIC90) for the labeled pathogens: Actinobacillus pleuropneumoniae, Pasteurella multocida, Streptococcus suis and Salmonella Choleraesuis for the 24 hour period between the dosing intervals. The MIC90 for Salmonella Choleraesuis (1 µg/mL) is higher than the other three pathogens and plasma concentrations exceed this value for the entire dosing interval only after the 2.27 mg/lb (5 mg/kg) BW dose.

Comparative Bioavailability Summary

The current EXCENEL RTU EZ Sterile Suspension formulation replaces a previously approved formulation. The previously approved EXCENEL RTU EZ product was a reformulation of another ceftiofur hydrochloride injectable product, EXCENEL RTU Sterile Suspension (NADA 140-890). Comparable plasma concentrations of ceftiofur administered as EXCENEL RTU Sterile Suspension or the reformulated EXCENEL RTU EZ Sterile Suspension were demonstrated in a comparative two-treatment, two-period crossover relative bioavailability study in swine. Products were administered via intramuscular (IM) injection into the neck, using alternating sides during periods 1 and 2. A summary of average plasma pharmacokinetic (PK) parameters in swine after a single IM administration of EXCENEL RTU Sterile Suspension and EXCENEL RTU EZ Sterile Suspension at a dose of 2.27 mg CE/lb (5 mg CE/kg) BW is provided in Table 1.

Table 1: Comparative treatment values (arithmetic mean ± SD) for the plasma PK estimates of total ceftiofur (parent compound plus desfuroylceftiofur metabolites) in swine following an IM administration of 2.27 mg CE/lb (5.0 mg CE/kg) BW, as either EXCENEL RTU (reference article) or as EXCENEL RTU EZ Sterile Suspension (test article).
PK Parameter | EXCENEL RTU | EXCENEL RTU EZ
Cmax (µg/mL) | 18.2 ± 4.09 | 19.7 ± 3.39
AUC0-LOQ (µg*h/mL) | 257 ± 57.1 | 263 ± 54.8
tmax (h) | 1.5 ± 0.49 | 1.5 ± 0.73
t1/2 (h) | 20.0 ± 1.56 | 20.0 ± 1.82
t>0.2 (h) | 83.1 ± 10.3 | 82.5 ± 10.5
Cmax - maximum plasma concentration
AUC0-LOQ - the area under the plasma concentration vs. time curve from time of injection to the limit of quantification of the assay
tmax - the time after initial injection to when Cmax occurs
t1/2 - the plasma half life of the drug
t>0.2 - the time plasma concentrations remain above 0.2 µg/mL.

The standard bioequivalence (BE) criteria, based upon the exponentiated 90% confidence bounds about the ratio of treatment means, were met for the pivotal bioequivalence parameters, AUC0-LOQ and Cmax, when each formulation was administered to swine IM at a dose rate of 2.27 mg CE/lb (5 mg CE/kg) BW (Table 2).

Table 2: Back-transformed least squares (LS) means and 90% confidence interval (CI) for the two pivotal pharmacokinetic parameters, Cmax and AUC0-LOQ in swine following an IM administration of 2.27 mg CE/lb (5.0 mg CE/kg) BW, as either EXCENEL RTU (reference article) or as EXCENEL RTU EZ Sterile Suspension (test article).
PK Parameter | LS Mean Difference | 90% CI | BE [If the 90% CI of the LS mean difference is within the limits of 0.80 to 1.25, then the results support bioequivalence of treatment groups]
Cmax | 1.10 | 1.03 to 1.18 | Yes
AUC0-LOQ | 1.03 | 0.99 to 1.06 | Yes

In another comparative bioavailability PK study (previously reviewed under NADA 140-890), comparable plasma concentrations of ceftiofur, administered as EXCENEL RTU Sterile Suspension or as NAXCEL Sterile Powder, were demonstrated when each product was administered intramuscularly at the upper end of the label dose range [2.27 mg CE/lb (5.0 mg CE/kg) BW]. The bioequivalence criteria were met for the AUC0-LOQ, Cmax, and t>0.2 when both products were administered by an intramuscular injection to swine at a dose rate of 5 mg CE/kg BW.

The effectiveness of injection site volumes greater than 5 mL to 15 mL was supported by a comparison of the length of time (hours) that plasma concentrations remained above 0.2 μg/mL (t>0.2) between injection site volumes less than or equal to 5 mL and injection site volumes greater than 5 mL to 12 mL. Statistical analysis allowed for an extrapolation of these findings to 15 mL per site. The pharmacokinetic data demonstrated that 5 mg/kg administered IM at injection volumes from greater than 5 mL to 15 mL resulted in acceptable t>0.2 for the indication.

Cattle:

Ceftiofur administered as either ceftiofur sodium or ceftiofur hydrochloride is metabolized rapidly to desfuroylceftiofur, the primary metabolite. Administration of ceftiofur to cattle as either the sodium or hydrochloride salt provides effective concentrations of ceftiofur and desfuroylceftiofur metabolites in plasma above the MIC90 for the label BRD pathogens Mannheimia haemolytica, Pasteurella multocida and Histophilus somni for at least 48 hours. The relationship between plasma concentrations of ceftiofur and desfuroylceftiofur metabolites above the MIC90 in plasma and effectiveness has not been established for the treatment of bovine interdigital necrobacillosis (foot rot) associated with Fusobacterium necrophorum and Bacteroides melaninogenicus.

Comparative Bioavailability Summary

The current EXCENEL RTU EZ Sterile Suspension formulation replaces a previously approved formulation. The previously approved EXCENEL RTU EZ product was a reformulation of another ceftiofur hydrochloride injectable product, EXCENEL RTU Sterile Suspension (NADA 140-890). Comparable plasma concentrations of ceftiofur administered as EXCENEL RTU Sterile Suspension and the reformulated EXCENEL RTU EZ Sterile Suspension were demonstrated in two comparative two-treatment, two-period crossover relative bioavailability studies in cattle. Products were administered via intramuscular (IM) or subcutaneous (SC) injection, using alternating sides of the neck during periods 1 and 2. A summary of average plasma pharmacokinetic (PK) parameters in cattle after a single IM and SC administration of EXCENEL RTU Sterile Suspension and EXCENEL RTU EZ Sterile Suspension at a dose of 1.0 mg CE/lb (2.2 mg CE/kg) BW is provided in Table 3.

Table 3: Comparative treatment values (arithmetic mean ± SD) for the plasma PK estimates of total ceftiofur (parent compound plus desfuroylceftiofur metabolites) in cattle following an IM or SC administration of 1.0 mg CE/lb (2.2 mg CE/kg) BW, as either EXCENEL RTU (reference article) or as EXCENEL RTU EZ Sterile Suspension (test article).
PK Parameter | IM |  | SC
PK Parameter | EXCENEL RTU | EXCENEL RTU EZ | EXCENEL RTU | EXCENEL RTU EZ
Cmax (µg/mL) | 8.58 ± 1.50 | 9.25 ± 1.73 | 8.40 ± 1.42 | 9.19 ± 1.65
AUC0-LOQ (µg*h/mL) | 89.4 ± 13.8 | 88.5 ±17.0 | 86.7 ± 20.3 | 91.0 ± 20.2
tmax (h) | 1.71 ± 0.706 | 1.73 ± 0.489 | 2.08 ± 0.670 | 2.25 ± 0.872
t1/2 (h) | 32.0 ± 8.48 | 29.3 ± 7.35 | 34.0 ± 8.52 | 32.9 ± 6.91
t>0.2 (h): | 42.2 ± 6.20 | 41.2 ± 6.11 | 40.5 ± 5.28 | 41.5 ± 7.32
Cmax - maximum plasma concentration
AUC0-LOQ - the area under the plasma concentration vs. time curve from time of injection to the limit of quantification of the assay
tmax - the time after initial injection to when Cmax occurs
t1/2 - the plasma half life of the drug
t>0.2 - the time plasma concentrations remain above 0.2 µg/mL

The standard bioequivalence (BE) criteria, based upon the exponentiated 90% confidence bounds about the ratio of treatment means, were met for the pivotal bioequivalence parameters, AUC0-LOQ and Cmax, when each formulation was administered to cattle IM or SC at a dose rate of 1 mg CE/lb (2.2 mg CE/kg) BW (Table 4).

Table 4: Back-transformed least squares (LS) means and 90% confidence intervals (CI) for the two pivotal pharmacokinetic parameters, Cmax and AUC0-LOQ in cattle following an IM and SC administration of 1 mg CE/lb (2.2 mg CE/kg) BW, as either EXCENEL RTU (reference article) or as EXCENEL RTU EZ Sterile Suspension (test article).
PK Parameter | IM |  | SC
PK Parameter | LS Mean Difference | 90% CI | LS Mean Difference | 90% CI
Cmax | 1.08 | 1.00 to 1.16 | 1.09 | 1.02 to 1.18
AUC0-LOQ | 0.984 | 0.94 to 1.03 | 1.06 | 0.99 to 1.13

In another comparative bioavailability PK study (previously reviewed under NADA 140-890), comparable plasma concentrations of ceftiofur administered as EXCENEL RTU Sterile Suspension or as NAXCEL Sterile Powder were demonstrated when each product was administered intramuscularly or subcutaneously at the approved dose range of ceftiofur sodium [0.5 to 1 mg CE/lb (1.1 to 2.2 mg CE/kg) BW].

MICROBIOLOGY

EXCENEL RTU EZ Sterile Suspension is a ready-to-use formulation that contains the hydrochloride salt of ceftiofur. Ceftiofur is a broad-spectrum cephalosporin antibiotic active against Gram-positive and Gram-negative bacteria. Like other cephalosporins, ceftiofur is predominantly bactericidal in vitro, resulting in the inhibition of cell wall synthesis. In vitro activity of ceftiofur has been demonstrated against Actinobacillus pleuropneumoniae, Pasteurella multocida, and Salmonella Choleraesuis, three pathogens associated with swine respiratory disease. Similarly, in vitro activity of ceftiofur has been demonstrated against Mannheimia haemolytica, Pasteurella multocida, and Histophilus somni, the three major pathogens associated with bovine respiratory disease, and against Fusobacterium necrophorum and Bacteroides melaninogenicus, pathogenic anaerobic bacteria associated with bovine foot rot.

Utilizing data that included isolates from swine and cattle affected by respiratory disease, zone diameter and minimum inhibitory concentration (MIC) breakpoints were determined using standardized procedures from the Clinical and Laboratory Standards Institute (CLSI, formerly National Committee of Clinical Laboratory Standards) M31-A2. The CLSI-accepted interpretive criteria for ceftiofur against these Gram-negative pathogens are shown in Table 5.

Table 5: CLSI-accepted interpretive criteria for ceftiofur against swine and cattle respiratory pathogens. [These interpretive criteria are only intended for use when CLSI M31-A2 performance standards are used to determine antimicrobial susceptibility.]
Pathogen | Disk potency | Zone diameter interpretive standards (mm) |  |  | MIC breakpoint (µg/mL)
Pathogen | Disk potency | S | I | R | S | I | R
Actinobacillus pleuropneumoniae | 30 µg | ≥ 21 | 18 to 20 | ≤ 17 | ≤ 2.0 | 4.0 | ≥ 8.0
Pasteurella multocida | 30 µg | ≥ 21 | 18 to 20 | ≤ 17 | ≤ 2.0 | 4.0 | ≥ 8.0
Salmonella Choleraesuis | 30 µg | ≥ 21 | 18 to 20 | ≤ 17 | ≤ 2.0 | 4.0 | ≥ 8.0
Mannheimia haemolytica | 30 µg | ≥ 21 | 18 to 20 | ≤ 17 | ≤ 2.0 | 4.0 | ≥ 8.0
Pasteurella multocida | 30 µg | ≥ 21 | 18 to 20 | ≤ 17 | ≤ 2.0 | 4.0 | ≥ 8.0
Histophilus somni | 30 µg | ≥ 21 | 18 to 20 | ≤ 17 | ≤ 2.0 | 4.0 | ≥ 8.0
S – Susceptible
I – Intermediate
R – Resistant

EFFECTIVENESS

Swine:

Plasma concentrations of ceftiofur administered as EXCENEL RTU Sterile Suspension or as EXCENEL RTU EZ Sterile Suspension following intramuscular administration in swine were compared and found to be bioequivalent for AUC0-LOQ and Cmax. Therefore, EXCENEL RTU EZ Sterile Suspension has the same effectiveness profile as previously established for EXCENEL RTU Sterile Suspension. Because the effectiveness of cephalosporin antibiotics is dependent upon time above MIC, EXCENEL RTU EZ Sterile Suspension is considered effective for the treatment/control of swine respiratory disease.

Cattle:

Plasma concentrations of ceftiofur administered as EXCENEL RTU Sterile Suspension or as EXCENEL RTU EZ Sterile Suspension following intramuscular or subcutaneous administration in cattle were compared and found to be bioequivalent for AUC0-LOQ and Cmax. Therefore, EXCENEL RTU EZ Sterile Suspension has the same effectiveness profile as previously established for EXCENEL RTU Sterile Suspension. Because the effectiveness of cephalosporin antibiotics is dependent upon time above MIC, EXCENEL RTU EZ Sterile Suspension is considered effective for the labeled indications.

ANIMAL SAFETY

Swine:

Evaluation of target animal safety in swine was based on a PK comparison between the reformulated EXCENEL RTU EZ Sterile Suspension and EXCENEL RTU Sterile Suspension. Ceftiofur administered to swine as the reformulated EXCENEL RTU EZ Sterile Suspension at a dose of 5 mg CE/kg BW by IM injection was demonstrated to be bioequivalent to a corresponding IM injection of EXCENEL RTU Sterile Suspension based upon comparability of their respective AUC0-LOQ and Cmax values (see EFFECTIVENESS section). Because of the demonstrated blood level bioequivalence, this study confirms the systemic safety of the reformulated EXCENEL RTU EZ Sterile Suspension in swine when administered by IM injection at a dose of 5 mg CE/kg BW for three consecutive days.

Injection site tissue tolerance and resolution were evaluated after administering EXCENEL RTU EZ Sterile Suspension by intramuscular injection to 8 young pigs with at least the maximum proposed volume of 5 mL per injection site once daily for three consecutive days. Each injection was administered in a different location on the neck, and injection sites alternated between the left and right sides. General health and injection sites were evaluated through 42 days after the first treatment. No test articlerelated health issues were observed. Mild swelling, erythema, and firmness was observed in a very small number of occasions (≤ 2% of total observations). No swelling was observed from 3 days after the last injection through the end of the study. Grossly visible discoloration of the injection site and histopathologic changes consistent with inflammation were noted in treated pigs necropsied 7 days or 14 days after injection.

A second injection site tissue tolerance study was conducted in 16 adult commercial crossbred pigs to evaluate the administration of EXCENEL RTU EZ Sterile Suspension by intramuscular injection with a maximum dose volume of 15 mL per injection site once daily for three consecutive days. Each injection was administered in a different location on the neck and injection sites alternated between the left and right sides. General health and injection sites were evaluated through 42 days after the first treatment. No test article-related health issues were observed. No swelling, erythema, or firmness were observed during the study. Gross necropsy and histopathologic changes consistent with inflammation were noted in treated pigs necropsied up to 42 days after injection.

Cattle:

Evaluation of target animal safety in cattle was based on two PK studies comparing the reformulated EXCENEL RTU EZ Sterile Suspension and EXCENEL RTU Sterile Suspension (one study comparing IM administration and one study comparing SC administration). In both studies, ceftiofur, when administered to cattle at a dose of 2.2 mg CE/kg BW of the reformulated EXCENEL RTU EZ Sterile Suspension, was demonstrated to be bioequivalent to a 2.2 mg CE/kg BW dose of EXCENEL RTU Sterile Suspension (see EFFECTIVENESS section). Because of the demonstrated blood-level bioequivalence, these studies confirm systemic safety of the reformulated EXCENEL RTU EZ Sterile Suspension when administered either IM or SC at a dose of 2.2 mg CE/kg BW for five consecutive days.

Injection site tissue tolerance and lesion resolution were evaluated after administration of the reformulated EXCENEL RTU EZ Sterile Suspension by intramuscular and subcutaneous injections to 16 growing cattle (8 cattle for each route) at the maximum volume of 15 mL per injection site, once daily for five consecutive days. Each injection was administered in a different location on the neck and injection sites alternated between the left and right sides. General health and injection sites were evaluated through necropsy (up to 42 days after the first dose). Animals were euthanized on Day 7, 14, 28, or 42 (two calves at each time point). No test article-related health issues were observed. Injection site reactions consisted of firmness and swelling at the injection sites. Injection site swelling was observed in 4/1030 (0.4%) of IM injection site observations and in 606/1029 (58.9%) of SC injection site observations. Swelling progressively decreased over time, and was still present in both animals injected SC that were necropsied on Day 42. Grossly visible discoloration of the injection site and/or histopathologic changes consistent with inflammation were noted through Day 42 in SC and IM injection sites.

TISSUE RESIDUE DEPLETION

Swine:

Radiolabeled residue metabolism studies established tolerances for ceftiofur residues in swine kidney, liver and muscle. The tolerances for ceftiofur residues are 0.25 ppm in kidney, 3 ppm in liver and 2 ppm in muscle.
A pivotal tissue residue decline study was conducted in swine. In this study, pigs received 2.27 mg of ceftiofur per lb body weight (5 mg of ceftiofur per kg body weight) per day for three consecutive days with an injection volume of 5 mL per site. Ceftiofur residues in edible tissues were less than the tolerances for ceftiofur at 4 days after dosing.
A second pivotal tissue residue decline study was conducted in large swine. In this study, animals received 3 consecutive once daily doses of EXCENEL RTU EZ Sterile Suspension by intramuscular injection at a dose rate of 2.27 mg of ceftiofur per lb body weight (5 mg CFAE/kg BW) with a maximum injection volume of 15 mL per injection site. Ceftiofur residues in tissues were below the tolerance in kidney by 6 days after dosing.
Collectively, the data from these two studies support a 4-day pre-slaughter withdrawal period in swine receiving injection site volumes less than or equal to 5 mL and a 6-day withdrawal period when receiving injection site volumes greater than 5 mL up to 15 mL per injection site.

Cattle:

A radiolabeled residue metabolism study established tolerances for ceftiofur residues in cattle kidney, liver and muscle. A separate study established the tolerance for ceftiofur residues in milk. The tolerances for ceftiofur residues are 0.4 ppm in kidney, 2 ppm in liver, 1 ppm in muscle and 0.1 ppm in milk.

Two pivotal tissue residue decline studies were conducted in cattle. Cattle received either a subcutaneous injection or intramuscular injection of 1 mg of ceftiofur per lb body weight (2.2 mg per kg body weight). In both studies, ceftiofur residues in tissues were less than the tolerances for ceftiofur residues in tissues such as the kidney and muscle by 4 days after dosing. These data collectively support a 4-day pre-slaughter withdrawal period when used according to label directions.

STORAGE CONDITIONS

Store at controlled room temperature 20° to 25°C (68° to 77°F); excursions permitted 15° to 40°C (59° to 104°F). Protect from freezing. Shake well before using. Contents should be used within 42 days after the first dose is removed.

HOW SUPPLIED

EXCENEL RTU EZ Sterile Suspension is available in 100 mL and 250 mL vials.

Approved by FDA under NADA # 141-288
Revised: July 2022
zoetis
Distributed by:
Zoetis Inc.
Kalamazoo, MI 49007
50175402